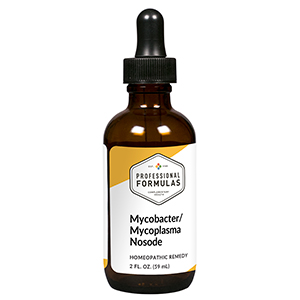 DRUG LABEL: Mycobacter/Mycoplasma Nosode
NDC: 63083-4009 | Form: LIQUID
Manufacturer: Professional Complementary Health Formulas
Category: homeopathic | Type: HUMAN OTC DRUG LABEL
Date: 20190815

ACTIVE INGREDIENTS: ARSENIC TRIIODIDE 30 [hp_X]/59 mL; SULFURIC ACID 30 [hp_X]/59 mL; STRYCHNOS NUX-VOMICA SEED 100 [hp_X]/59 mL; SULFUR 100 [hp_X]/59 mL; BACILLUS ANTHRACIS IMMUNOSERUM RABBIT 30 [hp_X]/59 mL; MYCOBACTERIUM ABSCESSUS 30 [hp_X]/59 mL; MYCOBACTERIUM AVIUM 30 [hp_X]/59 mL; MYCOBACTERIUM AVIUM SUBSP. PARATUBERCULOSIS 30 [hp_X]/59 mL; MYCOPLASMA PNEUMONIAE 30 [hp_X]/59 mL
INACTIVE INGREDIENTS: ALCOHOL; WATER

N9

ACTIVE INGREDIENTS

Arsenicum iodatum 30X
Sulphuricum acidum 30X
Nux vomica 100X
Sulphur 100X
and all the following at 30X, 60X, 100X:
Anthracinum
Mycobacterium abscessus
Mycobacterium avium-intracellulare
Mycobacterium chelonae
Mycobacterium fortuitum
Mycobacterium paratuberculosis
Mycoplasma arthritidis
Mycoplasma fermentans
Mycoplasma genitalium
Mycoplasma pneumoniae

QUESTIONS

Professional Formulas

PO Box 2034 Lake Oswego, OR 97035

INDICATIONS

For the temporary relief of cough, minor sore throat, occasional headache, runny nose, tiredness, lack of appetite, or feelings of discomfort or uneasiness.*

PURPOSE

*Claims based on traditional homeopathic practice, not accepted medical evidence. Not FDA evaluated.

WARNINGS

Severe or persistent symptoms may be a sign of a serious condition. Consult a doctor promptly if symptoms persist or are accompanied by a fever. Keep out of the reach of children. In case of overdose, get medical help or contact a poison control center right away. If pregnant or breastfeeding, ask a healthcare professional before use.

Keep out of the reach of children.

PREGNANCY OR BREAST FEEDING

If pregnant or breastfeeding, ask a healthcare professional before use.

DIRECTIONS

Place drops under tongue 30 minutes before/after meals. Adults and children 12 years and over: Take 10 to 15 drops once weekly or monthly. If mild symptoms are present, take 10 drops up to 3 times per day. Consult a physician for use in children under 12 years of age.

OTHER INFORMATION

Tamper resistant. If seal is broken, do not use. After opening, close container tightly and store at room temperature away from heat.

INACTIVE INGREDIENTS

20% ethanol, purified water.

LABEL

Est 1985

Professional Formulas

Complementary Health

Mycobacter/Mycoplasma Nosode

Homeopathic Remedy

2 FL. OZ. (59 mL)